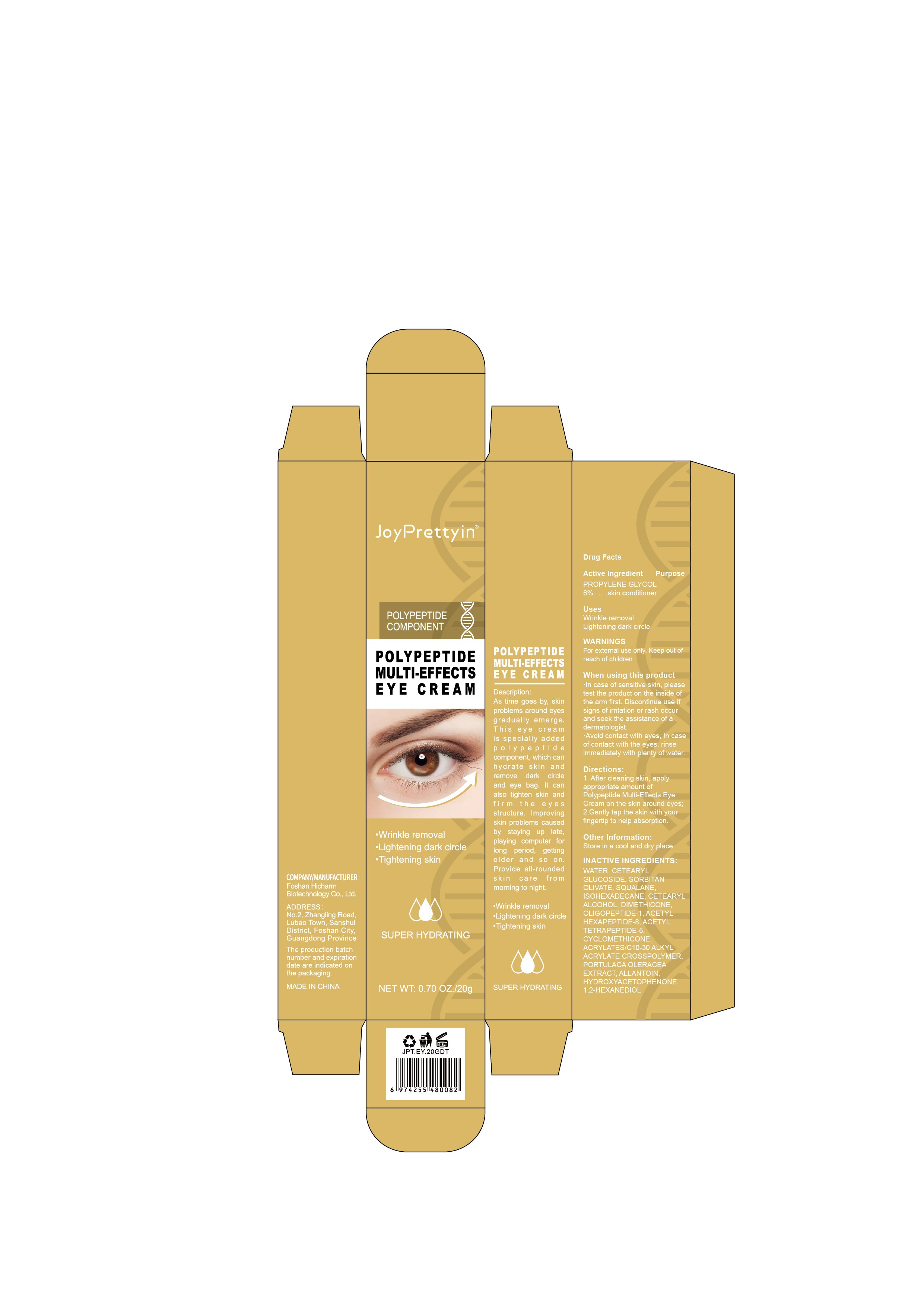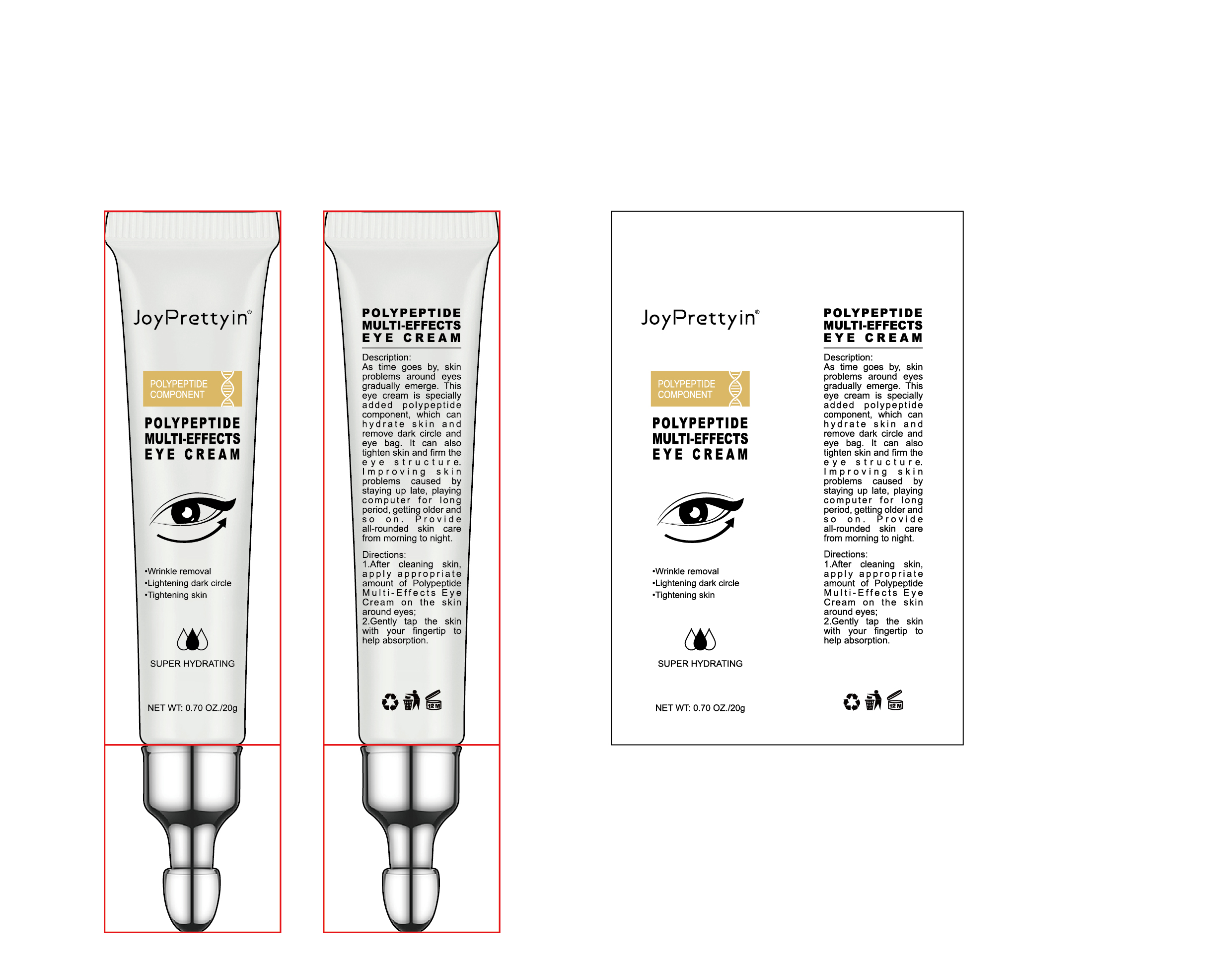 DRUG LABEL: Joypretty Polypeptidemulti-Effectseye Cream
NDC: 84186-008 | Form: CREAM
Manufacturer: Guangzhou Bonnieco Cosmetics Co., Ltd
Category: otc | Type: HUMAN OTC DRUG LABEL
Date: 20240401

ACTIVE INGREDIENTS: PROPYLENE GLYCOL 6 g/100 g
INACTIVE INGREDIENTS: CETOSTEARYL ALCOHOL; CYCLOMETHICONE; SQUALANE; WATER; HYDROXYACETOPHENONE; ACETYL TETRAPEPTIDE-5; SORBITAN OLIVATE; ACETYL HEXAPEPTIDE-8; 1,2-HEXANEDIOL; ISOHEXADECANE; DIMETHICONE; ACRYLATES/C10-30 ALKYL ACRYLATE CROSSPOLYMER (60000 MPA.S); ALLANTOIN; CETEARYL GLUCOSIDE; PURSLANE

84186-008

Active Ingredient

PROPYLENE GLYCOL 6%

Purpose

skin conditioner

Use

Wrinkle removal Lightening dark circle

Warnings

For external use only. Keep out ofreach of childre

Do not use

the arm first. Discontinue use ifsigns of irritation or rash occurand seek the assistance of adermatologist.

When Using

In case of contact with the eyes, rinse immediately with plenty of water.

Stop Use

If discomfort arises, please immediately stop using the product and seek the assistance of a dermatologist.

Ask Doctor

If discomfort arises, please immediately stop using the product and seek the assistance of a dermatologist.

Keep Oot Of Reach Of Children

Keep out of reach of children. If swallowed call emergency services.

Directions

1.After cleaning skin,apply appropriateamount of PolypeptideMulti-Effects EyeCream on the skinaround eyes; 2.Gently tap the skinwith your fingertip tohelp absorption.

Other information

Store in a cool and dry place

Inactive ingredients

WATER, PROPYLENE GLYCOL, CETEARYL GLUCOSIDE, SORBITAN OLIVATE, SQUALANE, ISOHEXADECANE, CETEARYL ALCOHOL, DIMETHICONE, OLIGOPEPTIDE-1, ACETYL HEXAPEPTIDE-8, ACETYL TETRAPEPTIDE-5, CYCLOMETHICONE, ACRYLATES/C10-30 ALKYL ACRYLATE CROSSPOLYMER, PORTULACA OLERACEA EXTRACT, ALLANTOIN, HYDROXYACETOPHENONE, 1,2-HEXANEDIOL